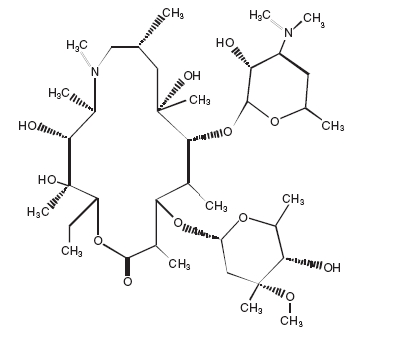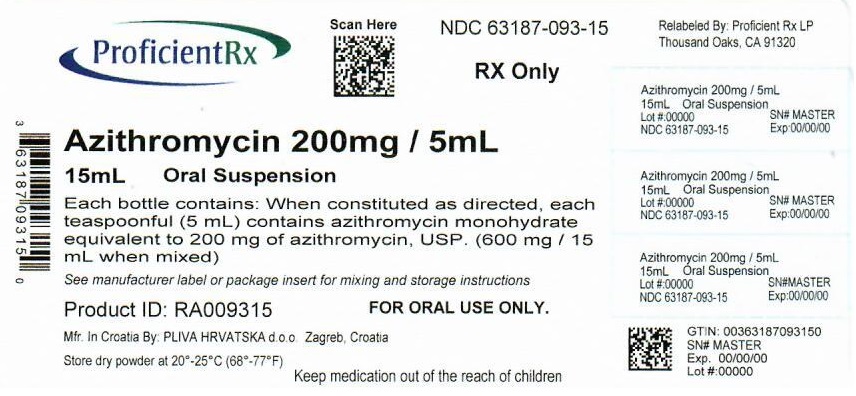 DRUG LABEL: Azithromycin
NDC: 63187-093 | Form: POWDER, FOR SUSPENSION
Manufacturer: Proficient Rx LP
Category: prescription | Type: HUMAN PRESCRIPTION DRUG LABEL
Date: 20240401

ACTIVE INGREDIENTS: AZITHROMYCIN MONOHYDRATE 200 mg/5 mL
INACTIVE INGREDIENTS: DIMETHYLAMINOETHYL METHACRYLATE - BUTYL METHACRYLATE - METHYL METHACRYLATE COPOLYMER; SILICON DIOXIDE; FD&C RED NO. 40; HYDROXYPROPYL CELLULOSE (1600000 WAMW); SUCROSE; SODIUM PHOSPHATE, TRIBASIC, ANHYDROUS; XANTHAN GUM

AZITHROMYCIN FOR ORAL SUSPENSION USP

To reduce the development of drug-resistant bacteria and maintain the effectiveness of azithromycin and other antibacterial drugs, azithromycin for oral suspension should be used only to treat or prevent infections that are proven or strongly suspected to be caused by bacteria.

DESCRIPTION

Azithromycin for oral suspension USP contains the active ingredient azithromycin, USP, an azalide, a subclass of macrolide antibiotics, for oral administration. Azithromycin, USP has the chemical name (2R,3S,4R,5R,8R, 10R,11R,12S,13S,14R)-13-[(2,6-dideoxy-3-C-methyl-3-O-methyl-α-L-ribo-hexopyranosyl) oxy]-2-ethyl-3,4,10-trihydroxy-3,5,6,8,10,12,14-heptamethyl-11-[[3,4,6-trideoxy-3- (dimethylamino)-β-D-xylo-hexopyranosyl]oxy]-1-oxa-6-azacyclopentadecan-15-one. Azithromycin, USP is derived from erythromycin; however, it differs chemically from erythromycin in that a methyl-substituted nitrogen atom is incorporated into the lactone ring.

Azithromycin, USP has the following structural formula:

C38H72N2O12 M.W. 749.0

Azithromycin, USP, as the monohydrate, is a white crystalline powder with a molecular formula of C38H72N2O12•H2O and a molecular weight of 767.0.

Azithromycin for oral suspension USP is supplied in bottles containing azithromycin monohydrate powder equivalent to 300 mg, 600 mg, 900 mg or 1200 mg azithromycin, USP per bottle and the following inactive ingredients: ammonio methacrylate copolymer, banana flavor, cherry flavor, colloidal silicon dioxide, FD&C Red No. 40, hydroxypropyl cellulose, sucrose, tribasic sodium phosphate anhydrous, vanilla flavor, and xanthan gum. After constitution, each 5 mL of suspension contains 100 mg or 200 mg of azithromycin, USP.

CLINICAL PHARMACOLOGY

Pharmacokinetics

Following oral administration of a single 500 mg dose (two 250 mg tablets) to 36 fasted healthy male volunteers, the mean (SD) pharmacokinetic parameters were AUC0-72 = 4.3 (1.2) mcg·h/mL; Cmax = 0.5 (0.2) mcg/mL; Tmax = 2.2 (0.9) hours.

With a regimen of 500 mg (two 250 mg capsules*) on day 1, followed by 250 mg daily (one 250 mg capsule) on days 2 through 5, the pharmacokinetic parameters of azithromycin in plasma in healthy young adults (18 to 40 years of age) are portrayed in the chart below. Cmin and Cmax remained essentially unchanged from day 2 through day 5 of therapy.

Pharmacokinetic Parameters (Mean) | Total n = 12; Day 1 | Day 5
Cmax (mcg/mL) | 0.41 | 0.24
Tmax (h) | 2.5 | 3.2
AUC0-24 (mcg·h/mL) | 2.6 | 2.1
Cmin (mcg/mL) | 0.05 | 0.05
Urinary Excret. (% dose) | 4.5 | 6.5
*Azithromycin 250 mg tablets are bioequivalent to 250 mg capsules in the fasted state. Azithromycin 250 mg capsules are no longer commercially available.

In a two-way crossover study, 12 adult healthy volunteers (6 males, 6 females) received 1,500 mg of azithromycin administered in single daily doses over either 5 days (two 250 mg tablets on day 1, followed by one 250 mg tablet on days 2 to 5) or 3 days (500 mg per day for days 1 to 3). Due to limited serum samples on day 2 (3 day regimen) and days 2 to 4 (5 day regimen), the serum concentration-time profile of each subject was fit to a 3 compartment model and the AUC0-∞ for the fitted concentration profile was comparable between the 5 day and 3 day regimens.

 | 3 Day Regimen |  | 5 Day Regimen
Pharmacokinetic Parameter; [mean (SD)] | Day 1 | Day 3 | Day 1 | Day 5
Cmax (serum, mcg/mL) | 0.44 (0.22) | 0.54 (0.25) | 0.43 (0.20) | 0.24 (0.06)
Serum AUC0-∞ (mcg·hr/mL) | 17.4 (6.2) |  | 14.9 (3.1)
Serum T1/2 | 71.8 hr |  | 68.9 hr

Median azithromycin exposure (AUC0-288) in mononuclear (MN) and polymorphonuclear (PMN) leukocytes following either the 5 day or 3 day regimen was more than a 1000 fold and 800 fold greater than in serum, respectively. Administration of the same total dose with either the 5 day or 3 day regimen may be expected to provide comparable concentrations of azithromycin within MN and PMN leukocytes.

Two azithromycin 250 mg tablets are bioequivalent to a single 500 mg tablet.

Absorption

The absolute bioavailability of azithromycin 250 mg capsules is 38%.

In a two-way crossover study in which 12 healthy subjects received a single 500 mg dose of azithromycin (two 250 mg tablets) with or without a high fat meal, food was shown to increase Cmax by 23% but had no effect on AUC.

When azithromycin suspension was administered with food to 28 adult healthy male subjects, Cmax increased by 56% and AUC was unchanged.

The AUC of azithromycin was unaffected by coadministration of an antacid containing aluminum and magnesium hydroxide with azithromycin capsules; however, the Cmax was reduced by 24%. Administration of cimetidine (800 mg) two hours prior to azithromycin had no effect on azithromycin absorption.

Distribution

The serum protein binding of azithromycin is variable in the concentration range approximating human exposure, decreasing from 51% at 0.02 mcg/mL to 7% at 2 mcg/mL.

Following oral administration, azithromycin is widely distributed throughout the body with an apparent steady-state volume of distribution of 31.1 L/kg. Greater azithromycin concentrations in tissues than in plasma or serum were observed. High tissue concentrations should not be interpreted to be quantitatively related to clinical efficacy. The antimicrobial activity of azithromycin is pH related and appears to be reduced with decreasing pH. However, the extensive distribution of drug to tissues may be relevant to clinical activity.

Selected tissue (or fluid) concentration and tissue (or fluid) to plasma/serum concentration ratios are shown in the following table:

AZITHROMYCIN CONCENTRATIONS FOLLOWING A 500 mg DOSE (TWO 250 mg CAPSULES) IN ADULTS
TISSUE OR FLUID | TIME AFTER; DOSE (h) | TISSUE OR FLUID CONCENTRATION; (mcg/g or mcg/mL) | CORRESPONDING PLASMA OR SERUM; LEVEL (mcg/mL) | TISSUE (FLUID); PLASMA (SERUM); RATIO
SKIN | 72 to 96 | 0.4 | 0.012 | 35
LUNG | 72 to 96 | 4 | 0.012 | > 100
SPUTUM | 2 to 4 | 1 | 0.64 | 2
SPUTUM | 10 to 12 | 2.9 | 0.1 | 30
TONSIL | 9 to 18 | 4.5 | 0.03 | > 100
TONSIL | 180 | 0.9 | 0.006 | > 100
CERVIX | 19 | 2.8 | 0.04 | 70

The extensive tissue distribution was confirmed by examination of additional tissues and fluids (bone, ejaculum, prostate, ovary, uterus, salpinx, stomach, liver, and gallbladder). As there are no data from adequate and well-controlled studies of azithromycin treatment of infections in these additional body sites, the clinical importance of these tissue concentration data is unknown.

Following a regimen of 500 mg on the first day and 250 mg daily for 4 days, only very low concentrations were noted in cerebrospinal fluid (less than 0.01 mcg/mL) in the presence of non-inflamed meninges.

Metabolism

In vitro and in vivo studies to assess the metabolism of azithromycin have not been performed.

Elimination

Plasma concentrations of azithromycin following single 500 mg oral and i.v. doses declined in a polyphasic pattern with a mean apparent plasma clearance of 630 mL/min and terminal elimination half-life of 68 hours. The prolonged terminal half-life is thought to be due to extensive uptake and subsequent release of drug from tissues.

Biliary excretion of azithromycin, predominantly as unchanged drug, is a major route of elimination. Over the course of a week, approximately 6% of the administered dose appears as unchanged drug in urine.

Special Populations

Renal Insufficiency

Azithromycin pharmacokinetics were investigated in 42 adults (21 to 85 years of age) with varying degrees of renal impairment. Following the oral administration of a single 1,000 mg dose of azithromycin, mean Cmax and AUC0-120 increased by 5.1% and 4.2%, respectively in subjects with mild to moderate renal impairment (GFR 10 to 80 mL/min) compared to subjects with normal renal function (GFR > 80 mL/min). The mean Cmax and AUC0-120 increased 61% and 35%, respectively in subjects with severe renal impairment (GFR < 10 mL/min) compared to subjects with normal renal function (GFR >80 mL/min) (see DOSAGE AND ADMINISTRATION).

Hepatic Insufficiency

The pharmacokinetics of azithromycin in subjects with hepatic impairment have not been established.

Gender

There are no significant differences in the disposition of azithromycin between male and female subjects. No dosage adjustment is recommended based on gender.

Geriatric Patients

When studied in healthy elderly subjects aged 65 to 85 years, the pharmacokinetic parameters of azithromycin in elderly men were similar to those in young adults; however, in elderly women, although higher peak concentrations (increased by 30 to 50%) were observed, no significant accumulation occurred.

Pediatric Patients

In two clinical studies, azithromycin for oral suspension was dosed at 10 mg/kg on day 1, followed by 5 mg/kg on days 2 through 5 to two groups of pediatric patients (aged 1 to 5 years and 5 to 15 years, respectively). The mean pharmacokinetic parameters on day 5 were Cmax = 0.216 mcg/mL, Tmax = 1.9 hours, and AUC0-24 = 1.822 mcg·hr/mL for the 1 to 5 year old group and were Cmax = 0.383 mcg/mL, Tmax = 2.4 hours, and AUC0-24 = 3.109 mcg·hr/mL for the 5 to 15 year old group.

Two clinical studies were conducted in 68 pediatric patients aged 3 to 16 years to determine the pharmacokinetics and safety of azithromycin for oral suspension. Azithromycin was administered following a low-fat breakfast.

The first study consisted of 35 pediatric patients treated with 20 mg/kg/day (maximum daily dose 500 mg) for 3 days of whom 34 patients were evaluated for pharmacokinetics.

In the second study, 33 pediatric patients received doses of 12 mg/kg/day (maximum daily dose 500 mg) for 5 days of whom 31 patients were evaluated for pharmacokinetics.

In both studies, azithromycin concentrations were determined over a 24 hour period following the last daily dose. Patients weighing above 25 kg in the 3 day study or 41.7 kg in the 5 day study received the maximum adult daily dose of 500 mg. Eleven patients (weighing 25 kg or less) in the first study and 17 patients (weighing 41.7 kg or less) in the second study received a total dose of 60 mg/kg. The following table shows pharmacokinetic data in the subset of pediatric patients who received a total dose of 60 mg/kg.

Pharmacokinetic Parameter; [mean (SD)] | 3 Day Regimen; (20 mg/kg x 3 days) | 5 Day Regimen; (12 mg/kg x 5 days)
n | 11 | 17
Cmax (mcg/mL) | 1.1 (0.4) | 0.5 (0.4)
Tmax (hr) | 2.7 (1.9) | 2.2 (0.8)
AUC0-24 (mcg·hr/mL) | 7.9 (2.9) | 3.9 (1.9)

The similarity of the overall exposure (AUC0-∞) between the 3 day and 5 day regimens in pediatric patients is unknown.

Single dose pharmacokinetics in pediatric patients given doses of 30 mg/kg have not been studied (see DOSAGE AND ADMINISTRATION).

Drug-Drug Interactions

Drug interaction studies were performed with azithromycin and other drugs likely to be coadministered. The effects of coadministration of azithromycin on the pharmacokinetics of other drugs are shown in Table 1 and the effect of other drugs on the pharmacokinetics of azithromycin are shown in Table 2.

Coadministration of azithromycin at therapeutic doses had a modest effect on the pharmacokinetics of the drugs listed in Table 1. No dosage adjustment of drugs listed in Table 1 is recommended when coadministered with azithromycin.

Coadministration of azithromycin with efavirenz or fluconazole had a modest effect on the pharmacokinetics of azithromycin. Nelfinavir significantly increased the Cmax and AUC of azithromycin. No dosage adjustment of azithromycin is recommended when administered with drugs listed in Table 2 (see PRECAUTIONS, Drug Interactions).

Table 1. Drug Interactions: Pharmacokinetic Parameters for Coadministered Drugs in the Presence of Azithromycin
Coadministered; Drug | Dose of; Coadministered Drug | Dose of Azithromycin | n | Ratio (with/without azithromycin) of Coadministered Drug Pharmacokinetic Parameters; (90% CI); No Effect = 1
Coadministered; Drug | Dose of; Coadministered Drug | Dose of Azithromycin | n | Mean Cmax | Mean AUC
Atorvastatin | 10 mg/day x 8 days | 500 mg/day PO on days 6 to 8 | 12 | 0.83; (0.63 to 1.08) | 1.01; (0.81 to 1.25)
Carbamazepine | 200 mg/day x 2 days, then 200 mg BID x 18 days | 500 mg/day PO for days 16 to 18 | 7 | 0.97; (0.88 to 1.06) | 0.96; (0.88 to 1.06)
Cetirizine | 20 mg/day x 11 days | 500 mg PO on day 7, then 250 mg/day on days 8 to 11 | 14 | 1.03; (0.93 to 1.14) | 1.02; (0.92 to 1.13)
Didanosine | 200 mg PO BID x 21 days | 1,200 mg/day PO on days 8 to 21 | 6 | 1.44; (0.85 to 2.43) | 1.14; (0.83 to 1.57)
Efavirenz | 400 mg/day x 7 days | 600 mg PO on day 7 | 14 | 1.04 | 0.95
Fluconazole | 200 mg PO single dose | 1,200 mg PO single dose | 18 | 1.04; (0.98 to 1.11) | 1.01; (0.97 to 1.05)
Indinavir | 800 mg TID x 5 days | 1,200 mg PO on day 5 | 18 | 0.96; (0.86 to 1.08) | 0.9; (0.81 to 1)
Midazolam | 15 mg PO on day 3 | 500 mg/day PO x 3 days | 12 | 1.27; (0.89 to 1.81) | 1.26; (1.01 to 1.56)
Nelfinavir | 750 mg TID x 11 days | 1,200 mg PO on day 9 | 14 | 0.90; (0.81 to 1.01) | 0.85; (0.78 to 0.93)
Rifabutin | 300 mg/day x 10 days | 500 mg PO on day 1, then 250 mg/day on days 2 to 10 | 6 | See footnote below | NA
Sildenafil | 100 mg on days 1 and 4 | 500 mg/day PO x 3 days | 12 | 1.16; (0.86 to 1.57) | 0.92; (0.75 to 1.12)
Theophylline | 4 mg/kg I.V. on days 1, 11, 25 | 500 mg PO on day 7, then 250 mg/day on days 8 to 11 | 10 | 1.19; (1.02 to 1.40) | 1.02; (0.86 to 1.22)
Theophylline | 300 mg PO BID x 15 days | 500 mg PO on day 6, then 250 mg/day on days 7 to 10 | 8 | 1.09; (0.92 to 1.29) | 1.08; (0.89 to 1.31)
Triazolam | 0.125 mg on day 2 | 500 mg PO on day1, then 250 mg/day; on day 2 | 12 | 1.06 | 1.02
Trimethoprim/ Sulfamethoxazole | 160 mg/800 mg/day PO x 7 days | 1,200 mg PO on day 7 | 12 | 0.85; (0.75 to 0.97); /0.90; (0.78 to 1.03) | 0.87; (0.80 to 0.95); /0.96; (0.88 to 1.03)
Zidovudine | 500 mg/day PO x 21 days | 600 mg/day PO x 14 days | 5 | 1.12; (0.42 to 3.02) | 0.94; (0.52 to 1.70)
Zidovudine | 500 mg/day PO x 21 days | 1,200 mg/day PO x 14 days | 4 | 1.31; (0.43 to 3.97) | 1.30; (0.69 to 2.43)
NA - Not Available
Mean rifabutin concentrations one-half day after the last dose of rifabutin were 60 ng/mL when coadministered with azithromycin and 71 ng/mL when coadministered with placebo.

Table 2. Drug Interactions: Pharmacokinetic Parameters for Azithromycin in the Presence of Coadministered Drugs (see PRECAUTIONS, Drug Interactions)
Coadministered Drug | Dose of Coadministered Drug | Dose of Azithromycin | n | Ratio (with/without; coadministered drug) of Azithromycin Pharmacokinetic; Parameters (90% CI);; No Effect = 1
Coadministered Drug | Dose of Coadministered Drug | Dose of Azithromycin | n | Mean Cmax | Mean AUC
Efavirenz | 400 mg/day x 7 days | 600 mg PO on day 7 | 14 | 1.22; (1.04 to 1.42) | 0.92
Fluconazole | 200 mg PO single dose | 1,200 mg PO single dose | 18 | 0.82; (0.66 to 1.02) | 1.07; (0.94 to 1.22)
Nelfinavir | 750 mg TID x 11 days | 1,200 mg PO on day 9 | 14 | 2.36; (1.77 to 3.15) | 2.12; (1.80 to 2.50)
Rifabutin | 300 mg/day x 10 days | 500 mg PO on day 1, then 250 mg/day on days 2 to 10 | 6 | See footnote below | NA
NA - Not available

Mean azithromycin concentrations one day after the last dose were 53 ng/mL when coadministered with 300 mg daily rifabutin and 49 ng/mL when coadministered with placebo.

Pharmacodynamics

Cardiac Electrophysiology

QTc interval prolongation was studied in a randomized, placebo-controlled parallel trial in 116 healthy subjects who received either chloroquine (1000 mg) alone or in combination with azithromycin (500 mg, 1000 mg, and 1500 mg once daily). Coadministration of azithromycin increased the QTc interval in a dose-and concentration-dependent manner. In comparison to chloroquine alone, the maximum mean (95% upper confidence bound) increases in QTcF were 5

(10) ms, 7 (12) ms and 9 (14) ms with the coadministration of 500 mg, 1000 mg and 1500 mg azithromycin, respectively.

Microbiology

Mechanism of Action

Azithromycin binds to the 23S rRNA of the bacterial 50S ribosomal subunit. It blocks protein synthesis by inhibiting the transpeptidation/translocation step of protein synthesis and by inhibiting the assembly of the 50S ribosomal subunit.

Azithromycin concentrates in phagocytes and fibroblasts as demonstrated by in vitro incubation techniques. The ratio of intracellular to extracellular concentration was > 30 after one hour incubation. In vivo studies suggest that concentration in phagocytes may contribute to drug distribution to inflamed tissues.

Mechanism of Resistance

The most frequently encountered mechanism of resistance to azithromycin is modification of the 23S rRNA at positions corresponding to A2058 and A2059 in the Escherichia coli numbering system. In addition to cross resistance with other macrolides (erythromycin and clarithromycin), ribosomal modification may determine resistance to other antibiotic classes (lincosamides and streptogramins B) that bind to overlapping ribosomal sites.

Azithromycin has been shown to be active against most isolates of the following bacteria, both in vitro and in clinical infections (see INDICATIONS AND USAGE).

Gram-positive bacteria

Staphylococcus aureus

Streptococcus agalactiae

Streptococcus pneumoniae

Streptococcus pyogenes

Gram-negative bacteria

Haemophilus ducreyi

Haemophilus influenzae

Moraxella catarrhalis

Neisseria gonorrhoeae

“Other” bacteria

Chlamydophila pneumoniae

Chlamydia trachomatis

Mycoplasma pneumoniae

The following in vitro data are available, but their clinical significance is unknown.

At least 90% of the following bacteria exhibit an in vitro minimum inhibitory concentration (MIC) less than or equal to the azithromycin susceptible breakpoint of ≤ 4 mcg/mL. However, safety and effectiveness of azithromycin in treating clinical infections due to these bacteria have not been established in adequate and well-controlled trials.

Gram-positive bacteria

Beta-hemolytic streptococci (Groups C, F, G)

Viridans group streptococci

Gram-negative bacteria

Bordetella pertussis

Anaerobic bacteria

Peptostreptococcus species

Prevotella bivia

“Other” bacteria

Ureaplasma urealyticum

Legionella pneumophila

Susceptibility Testing Methods

When available, the results of in vitro susceptibility test results for antimicrobial drugs used in resident hospitals should be provided to the physician as periodic reports which describe the susceptibility profile of nosocomial and community-acquired pathogens. These reports may differ from susceptibility data obtained from outpatient use, but could aid the physician in selecting the most effective antimicrobial.

Dilution Techniques

Quantitative methods are used to determine antimicrobial minimum inhibitory concentrations (MICs). These MICs provide estimates of the susceptibility of bacteria to antimicrobial compounds. The MICs should be determined using a standardized procedure. Standardized procedures are based on a dilution method^1,2 (broth or agar) or equivalent with standardized inoculum concentration and standardized concentration of azithromycin powder. The MIC values should be interpreted according to criteria provided in Table 3.

Diffusion Techniques

Quantitative methods that require measurement of zone diameters also provide reproducible estimates of the susceptibility of bacteria to antimicrobial compounds. One such standardized procedure^2,3 requires the use of standardized inoculum concentration. This procedure uses paper disks impregnated with 15 mcg azithromycin to test the susceptibility of bacteria to azithromycin. The disk diffusion interpretive criteria are provided in Table 3.

Table 3. Susceptibility Test Interpretive Criteria for Azithromycin Susceptibility Test Result Interpretive Criteria
Pathogen | Minimum Inhibitory Concentrations (mcg/mL) |  |  | Disk Diffusion; (zone diameters in mm)
 | S | I | R | S | I | R
Haemophilus influenzae | ≤ 4 | -- | -- | ≥ 12 | -- | --
Staphylococcus aureus | ≤ 2 | 4 | ≥ 8 | ≥ 18 | 14 to 17 | ≤ 13
Streptococci including; S. pneumoniae | ≤ 0.5 | 1 | ≥ 2 | ≥ 18 | 14 to 17 | ≤ 13
Susceptibility to azithromycin must be tested in ambient air.

The ability to correlate MIC values and plasma drug levels is difficult as azithromycin concentrates in macrophages and tissues (see Clinical Pharmacology).

A report of “susceptible” indicates that the pathogen is likely to be inhibited if the antimicrobial compound reaches the concentrations usually achievable. A report of “intermediate” indicates that the result should be considered equivocal, and, if the microorganism is not fully susceptible to alternative, clinically feasible drugs, the test should be repeated. This category implies possible clinical applicability in body sites where the drug is physiologically concentrated or in situations where high dosage of drug can be used. This category also provides a buffer zone which prevents small uncontrolled technical factors from causing major discrepancies in interpretation. A report of “resistant” indicates that the pathogen is not likely to be inhibited if the antimicrobial compound reaches the concentrations usually achievable; other therapy should be selected.

Quality Control

Standardized susceptibility test procedures require the use of laboratory controls to monitor and ensure the accuracy and precision of supplies and reagents used in the assay, and the techniques of the individual performing the test. Standard azithromycin powder should provide the following range of MIC values noted in Table 4. For the diffusion technique using the azithromycin 15 mcg disk, the criteria in Table 4 should be achieved.

Table 4. Acceptable Quality Control Ranges for Azithromycin
QC Strain | Minimum Inhibitory Concentrations (mcg/mL) | Disk Diffusion; (zone diameters in mm)
Haemophilus influenzae; ATCC [ATCC = American Type Culture Collection] 49247 | 1 to 4 | 13 to 21
Staphylococcus aureus ATCC 29213 | 0.5 to 2 | •••
Staphylococcus aureus; ATCC 25923 | ••• | 21 to 26
Streptococcus pneumoniae; ATCC 49619 | 0.06 to 0.25 | 19 to 25
Susceptibility to azithromycin must be tested in ambient air

INDICATIONS AND USAGE

Azithromycin for oral suspension USP is indicated for the treatment of patients with mild to moderate infections (pneumonia: see WARNINGS) caused by susceptible strains of the designated microorganisms in the specific conditions listed below. As recommended dosages, durations of therapy and applicable patient populations vary among these infections, please see DOSAGE AND ADMINISTRATION for specific dosing recommendations.

Adults

Acute bacterial exacerbations of chronic obstructive pulmonary disease due to Haemophilus influenzae, Moraxella catarrhalis or Streptococcus pneumoniae.

Acute bacterial sinusitis due to Haemophilus influenzae, Moraxella catarrhalis or Streptococcus pneumoniae.

Community-acquired pneumonia due to Chlamydophila pneumoniae, Haemophilus influenzae, Mycoplasma pneumoniae or Streptococcus pneumoniae in patients appropriate for oral therapy.

NOTE: Azithromycin should not be used in patients with pneumonia who are judged to be inappropriate for oral therapy because of moderate to severe illness or risk factors such as any of the following:

patients with cystic fibrosis,

patients with nosocomially acquired infections,

patients with known or suspected bacteremia,

patients requiring hospitalization,

elderly or debilitated patients, or

patients with significant underlying health problems that may compromise their ability

to respond to their illness (including immunodeficiency or functional asplenia).

Pharyngitis/tonsillitis caused by Streptococcus pyogenes as an alternative to first-line therapy in individuals who cannot use first-line therapy.

NOTE: Penicillin by the intramuscular route is the usual drug of choice in the treatment of Streptococcus pyogenes infection and the prophylaxis of rheumatic fever. Azithromycin for oral suspension USP is often effective in the eradication of susceptible strains of Streptococcus pyogenes from the nasopharynx. Because some strains are resistant to azithromycin for oral suspension USP, susceptibility tests should be performed when patients are treated with azithromycin for oral suspension USP. Data establishing efficacy of azithromycin in subsequent prevention of rheumatic fever are not available.

Uncomplicated skin and skin structure infections due to Staphylococcus aureus, Streptococcus pyogenes, or Streptococcus agalactiae. Abscesses usually require surgical drainage.

Urethritis and cervicitis due to Chlamydia trachomatis or Neisseria gonorrhoeae.

Genital ulcer disease in men due to Haemophilus ducreyi (chancroid). Due to the small number of women included in clinical trials, the efficacy of azithromycin in the treatment of chancroid in women has not been established.

Azithromycin for oral suspension USP, at the recommended dose, should not be relied upon to treat syphilis. Antimicrobial agents used in high doses for short periods of time to treat non-gonococcal urethritis may mask or delay the symptoms of incubating syphilis. All patients with sexually-transmitted urethritis or cervicitis should have a serologic test for syphilis and appropriate cultures for gonorrhea performed at the time of diagnosis. Appropriate antimicrobial therapy and follow-up tests for these diseases should be initiated if infection is confirmed.

Appropriate culture and susceptibility tests should be performed before treatment to determine the causative organism and its susceptibility to azithromycin, USP. Therapy with azithromycin for oral suspension USP may be initiated before results of these tests are known; once the results become available, antimicrobial therapy should be adjusted accordingly.

To reduce the development of drug-resistant bacteria and maintain the effectiveness of azithromycin for oral suspension USP and other antibacterial drugs, azithromycin for oral suspension USP should be used only to treat or prevent infections that are proven or strongly suspected to be caused by susceptible bacteria. When culture and susceptibility information are available, they should be considered in selecting or modifying antibacterial therapy. In the absence of such data, local epidemiology and susceptibility patterns may contribute to the empiric selection of therapy.

Pediatric Patients

See PRECAUTIONS, Pediatric Use and CLINICAL STUDIES, Pediatric Patients.

Acute otitis media caused by Haemophilus influenzae, Moraxella catarrhalis or Streptococcus pneumoniae. (For specific dosage recommendation, see DOSAGE AND ADMINISTRATION.)

Community-acquired pneumonia due to Chlamydophila pneumoniae, Haemophilus influenzae, Mycoplasma pneumoniae or Streptococcus pneumoniae in patients appropriate for oral therapy. (For specific dosage recommendation, see DOSAGE AND ADMINISTRATION.)

NOTE: Azithromycin should not be used in pediatric patients with pneumonia who are judged to be inappropriate for oral therapy because of moderate to severe illness or risk factors such as any of the following:

patients with cystic fibrosis,

patients with nosocomially acquired infections,

patients with known or suspected bacteremia,

patients requiring hospitalization, or

patients with significant underlying health problems that may compromise their ability

to respond to their illness (including immunodeficiency or functional asplenia).

Pharyngitis/tonsillitis caused by Streptococcus pyogenes as an alternative to first-line therapy in individuals who cannot use first-line therapy. (For specific dosage recommendation, see DOSAGE AND ADMINISTRATION.)

NOTE: Penicillin by the intramuscular route is the usual drug of choice in the treatment of Streptococcus pyogenes infection and the prophylaxis of rheumatic fever. Azithromycin for oral suspension USP is often effective in the eradication of susceptible strains of Streptococcus pyogenes from the nasopharynx. Because some strains are resistant to azithromycin for oral suspension USP, susceptibility tests should be performed when patients are treated with azithromycin for oral suspension USP. Data establishing efficacy of azithromycin in subsequent prevention of rheumatic fever are not available.

Appropriate culture and susceptibility tests should be performed before treatment to determine the causative organism and its susceptibility to azithromycin. Therapy with azithromycin for oral suspension USP may be initiated before results of these tests are known; once the results become available, antimicrobial therapy should be adjusted accordingly.

CONTRAINDICATIONS

Azithromycin is contraindicated in patients with known hypersensitivity to azithromycin, erythromycin any macrolide or ketolide antibiotic. Azithromycin is contraindicated in patients with a history of cholestatic jaundice/hepatic dysfunction associated with prior use of azithromycin.

WARNINGS

Hypersensitivity

Serious allergic reactions, including angioedema, anaphylaxis, and dermatologic reactions including Stevens-Johnson syndrome and toxic epidermal necrolysis have been reported rarely in patients on azithromycin therapy. Although rare, fatalities have been reported (see CONTRAINDICATIONS). Despite initially successful symptomatic treatment of the allergic symptoms, when symptomatic therapy was discontinued, the allergic symptoms recurred soon thereafter in some patients without further azithromycin exposure. These patients required prolonged periods of observation and symptomatic treatment. The relationship of these episodes to the long tissue half-life of azithromycin and subsequent prolonged exposure to antigen is unknown at present.

If an allergic reaction occurs, the drug should be discontinued and appropriate therapy should be instituted. Physicians should be aware that reappearance of the allergic symptoms may occur when symptomatic therapy is discontinued.

Hepatotoxicity

Abnormal liver function, hepatitis, cholestatic jaundice, hepatic necrosis, and hepatic failure have been reported, some of which have resulted in death. Discontinue azithromycin immediately if signs and symptoms of hepatitis occur.

Treatment of Pneumonia

In the treatment of pneumonia, azithromycin has only been shown to be safe and effective in the treatment of community-acquired pneumonia due to Chlamydia pneumoniae, Haemophilusinfluenzae, Mycoplasma pneumoniae or Streptococcus pneumoniae in patients appropriate for oral therapy. Azithromycin should not be used in patients with pneumonia who are judged to be inappropriate for oral therapy because of moderate to severe illness or risk factors such as any of thefollowing: patients with cystic fibrosis, patients with nosocomially acquired infections, patients with known or suspected bacteremia, patients requiring hospitalization, elderly or debilitated patients, or patients with significant underlying health problems that may compromise their ability to respond totheir illness (including immunodeficiency or functional asplenia).

Clostridium Difficile-associated Diarrhea

Clostridium difficile-associated diarrhea (CDAD) has been reported with use of nearly all antibacterial agents, including azithromycin, and may range in severity from mild diarrhea to fatal colitis. Treatment with antibacterial agents alters the normal flora of the colon leading to overgrowth of C. difficile.

C. difficile produces toxins A and B which contribute to the development of CDAD. Hypertoxin producing strains of C. difficile cause increased morbidity and mortality, as these infections can be refractory to antimicrobial therapy and may require colectomy. CDAD must be considered in all patients who present with diarrhea following antibiotic use. Careful medical history is necessary since CDAD has been reported to occur over two months after the administration of antibacterial agents.

If CDAD is suspected or confirmed, ongoing antibiotic use not directed against C. difficile may need to be discontinued. Appropriate fluid and electrolyte management, protein supplementation, antibiotic treatment of C. difficile, and surgical evaluation should be instituted as clinically indicated.

QT Prolongation

Prolonged cardiac repolarization and QT interval, imparting a risk of developing cardiac arrhythmia and torsade de pointes, have been seen in treatment with macrolides, including azithromycin. Cases of torsade de pointes have been spontaneously reported during postmarketing surveillance in patients receiving azithromycin. Providers should consider the risk of QT prolongation which can be fatal when weighing the risks and benefits of azithromycin for at-risk groups including:

- patients with known prolongation of the QT interval, a history of torsade de pointes, congenital long QT syndrome, bradyarrhythmias or uncompensated heart failure
- patients on drugs known to prolong the QT interval
- patients with ongoing proarrhythmic conditions such as uncorrected hypokalemia or hypomagnesemia, clinically significant bradycardia, and in patients receiving Class IA (quinidine, procainamide) or Class III (dofetilide, amiodarone, sotalol) antiarrhythmic agents.

Elderly patients may be more susceptible to drug-associated effects on the QT interval.

PRECAUTIONS

General

Because azithromycin is principally eliminated via the liver, caution should be exercised when azithromycin is administered to patients with impaired hepatic function. Due to the limited data in subjects with GFR < 10 mL/min, caution should be exercised when prescribing azithromycin in these patients (see CLINICAL PHARMACOLOGY, Special Populations, Renal Insufficiency).

Exacerbation of symptoms of myasthenia gravis and new onset of myasthenic syndrome have been reported in patients receiving azithromycin therapy.

Prescribing azithromycin in the absence of a proven or strongly suspected bacterial infection or a prophylactic indication is unlikely to provide benefit to the patient and increases the risk of the development of drug-resistant bacteria.

Information for Patients

Azithromycin for oral suspension can be taken with or without food.

Patients should also be cautioned not to take aluminum- and magnesium-containing antacids and azithromycin simultaneously.

The patient should be directed to discontinue azithromycin immediately and contact a physician if any signs of an allergic reaction occur.

Patients should be counseled that antibacterial drugs including azithromycin should only be used to treat bacterial infections. They do not treat viral infections (e.g., the common cold). When azithromycin is prescribed to treat a bacterial infection, patients should be told that although it is common to feel better early in the course of the therapy, the medication should be taken exactly as directed. Skipping doses or not completing the full course of therapy may (1) decrease the effectiveness of the immediate treatment and (2) increase the likelihood that bacteria will develop resistance and will not be treatable by azithromycin or other antibacterial drugs in the future.

Diarrhea is a common problem caused by antibiotics which usually ends when the antibiotic is discontinued. Sometimes after starting treatment with antibiotics, patients can develop watery and bloody stools (with or without stomach cramps and fever) even as late as two or more months after having taken the last dose of the antibiotic. If this occurs, patients should contact their physician as soon as possible.

Drug Interactions

Coadministration of nelfinavir at steady-state with a single oral dose of azithromycin resulted in increased azithromycin serum concentrations. Although a dose adjustment of azithromycin is not recommended when administered in combination with nelfinavir, close monitoring for known side effects of azithromycin, such as liver enzyme abnormalities and hearing impairment, is warranted (see ADVERSE REACTIONS).

Although, in a study of 22 healthy men, a 5 day course of azithromycin did not affect the prothrombin time from a subsequently administered dose of warfarin, spontaneous postmarketing reports suggest that concomitant administration of azithromycin may potentiate the effects of oral anticoagulants. Prothrombin times should be carefully monitored while patients are receiving azithromycin and oral anticoagulants concomitantly.

Drug interaction studies were performed with azithromycin and other drugs likely to be coadministered (see CLINICAL PHARMACOLOGY, Drug-Drug Interactions). When used in therapeutic doses, azithromycin had a modest effect on the pharmacokinetics of atorvastatin, carbamazepine, cetirizine, didanosine, efavirenz, fluconazole, indinavir, midazolam, rifabutin, sildenafil, theophylline (intravenous and oral), triazolam, trimethoprim/sulfamethoxazole or zidovudine. Coadministration with efavirenz, or fluconazole had a modest effect on the pharmacokinetics of azithromycin. No dosage adjustment of either drug is recommended when azithromycin is coadministered with any of the above agents.

Interactions with the drugs listed below have not been reported in clinical trials with azithromycin; however, no specific drug interaction studies have been performed to evaluate potential drug-drug interaction. Nonetheless, they have been observed with macrolide products. Until further data are developed regarding drug interactions when azithromycin and these drugs are used concomitantly, careful monitoring of patients is advised:

Digoxin–elevated digoxin concentrations.

Ergotamine or dihydroergotamine–acute ergot toxicity characterized by severe peripheral vasospasm and dysesthesia.

Terfenadine, cyclosporine, hexobarbital and phenytoin concentrations.

Laboratory Test Interactions

There are no reported laboratory test interactions.

Carcinogenesis, Mutagenesis, Impairment of Fertility

Long-term studies in animals have not been performed to evaluate carcinogenic potential. Azithromycin has shown no mutagenic potential in standard laboratory tests: mouse lymphoma assay, human lymphocyte clastogenic assay, and mouse bone marrow clastogenic assay. No evidence of impaired fertility due to azithromycin was found.

Pregnancy

Teratogenic Effects

Pregnancy Category B

Reproduction studies have been performed in rats and mice at doses up to moderately maternally toxic dose concentrations (i.e., 200 mg/kg/day). These doses, based on a mg/m^2 basis, are estimated to be 4 and 2 times, respectively, the human daily dose of 500 mg. In the animal studies, no evidence of harm to the fetus due to azithromycin was found. There are, however, no adequate and well-controlled studies in pregnant women. Because animal reproduction studies are not always predictive of human response, azithromycin should be used during pregnancy only if clearly needed.

Nursing Mothers

It is not known whether azithromycin is excreted in human milk. Because many drugs are excreted in human milk, caution should be exercised when azithromycin is administered to a nursing woman.

Pediatric Use

See CLINICAL PHARMACOLOGY, INDICATIONS AND USAGE, and DOSAGE AND ADMINISTRATION.

Acute Otitis Media (total dosage regimen: 30 mg/kg, see DOSAGE AND ADMINISTRATION): Safety and effectiveness in the treatment of pediatric patients with otitis media under 6 months of age have not been established.

Acute Bacterial Sinusitis (dosage regimen: 10 mg/kg on Days 1 to 3): Safety and effectiveness in the treatment of pediatric patients with acute bacterial sinusitis under 6 months of age have not been established. Use of azithromycin for the treatment of acute bacterial sinusitis in pediatric patients (6 months of age or greater) is supported by adequate and well-controlled studies in adults, similar pathophysiology of acute sinusitis in adults and pediatric patients, and studies of acute otitis media in pediatric patients.

Community-Acquired Pneumonia (dosage regimen: 10 mg/kg on Day 1 followed by 5 mg/kg on Days 2 to 5): Safety and effectiveness in the treatment of pediatric patients with community-acquired pneumonia under 6 months of age have not been established. Safety and effectiveness for pneumonia due to Chlamydophilapneumoniae and Mycoplasma pneumoniae were documented in pediatric clinical trials. Safety and effectiveness for pneumonia due to Haemophilus influenzae and Streptococcus pneumoniae were not documented bacteriologically in the pediatric clinical trial due to difficulty in obtaining specimens. Use of azithromycin for these two microorganisms is supported, however, by evidence from adequate and well-controlled studies in adults.

Pharyngitis/Tonsillitis (dosage regimen: 12 mg/kg on Days 1 to 5): Safety and effectiveness in the treatment of pediatric patients with pharyngitis/tonsillitis under 2 years of age have not been established.

Studies evaluating the use of repeated courses of therapy have not been conducted (see CLINICAL PHARMACOLOGY and ANIMAL TOXICOLOGY).

Geriatric Use

Pharmacokinetic parameters in older volunteers (65 to 85 years old) were similar to those in younger volunteers (18 to 40 years old) for the 5 day therapeutic regimen. Dosage adjustment does not appear to be necessary for older patients with normal renal and hepatic function receiving treatment with this dosage regimen (see CLINICAL PHARMACOLOGY).

In multiple-dose clinical trials of oral azithromycin, 9% of patients were at least 65 years of age (458/4949) and 3% of patients (144/4949) were at least 75 years of age. No overall differences in safety or effectiveness were observed between these subjects and younger subjects, and other reported clinical experience has not identified differences in response between the elderly and younger patients, but greater sensitivity of some older individuals cannot be ruled out.

Elderly patients may be more susceptible to development of torsade de pointes arrhythmia than younger patients (see WARNINGS).

Azithromycin for oral suspension USP, 100 mg/5 mL contains 8.8 mg of sodium per 5 mL of constituted solution.

Azithromycin for oral suspension USP, 200 mg/5 mL contains 8.8 mg of sodium per 5 mL of constituted solution.

ADVERSE REACTIONS

In clinical trials, most of the reported side effects were mild to moderate in severity and were reversible upon discontinuation of the drug. Potentially serious side effects of angioedema and cholestatic jaundice were reported rarely. Approximately 0.7% of the patients (adults and pediatric patients) from the 5 day multiple-dose clinical trials discontinued azithromycin therapy because of treatment-related side effects. In adults given 500 mg/day for 3 days, the discontinuation rate due to treatment-related side effects was 0.6%. In clinical trials in pediatric patients given 30 mg/kg, either as a single dose or over 3 days, discontinuation from the trials due to treatment-related side effects was approximately 1% (see DOSAGE AND ADMINISTRATION). Most of the side effects leading to discontinuation were related to the gastrointestinal tract, e.g., nausea, vomiting, diarrhea, or abdominal pain (see CLINICAL STUDIES, Pediatric Patients).

Clinical

Adults

Multiple-dose regimens: Overall, the most common treatment-related side effects in adult patients receiving multiple-dose regimens of azithromycin were related to the gastrointestinal system with diarrhea/loose stools (4 to 5%), nausea (3%) and abdominal pain (2 to 3%) being the most frequently reported.

No other treatment-related side effects occurred in patients on the multiple-dose regimens of azithromycin with a frequency greater than 1%. Side effects that occurred with a frequency of 1% or less included the following:

Cardiovascular: Palpitations, chest pain.

Gastrointestinal: Dyspepsia, flatulence, vomiting, melena and cholestatic jaundice.

Genitourinary: Monilia, vaginitis and nephritis.

Nervous System: Dizziness, headache, vertigo and somnolence.

General: Fatigue.

Allergic: Rash, pruritus, photosensitivity and angioedema.

Single 1 gram dose regimen: Overall, the most common side effects in patients receiving a single-dose regimen of 1 gram of azithromycin were related to the gastrointestinal system and were more frequently reported than in patients receiving the multiple-dose regimen.

Side effects that occurred in patients on the single one-gram dosing regimen of azithromycin with a frequency of 1% or greater included diarrhea/loose stools (7%), nausea (5%), abdominal pain (5%), vomiting (2%), dyspepsia (1%) and vaginitis (1%).

Single 2 gram dose regimen: Overall, the most common side effects in patients receiving a single 2 gram dose of azithromycin were related to the gastrointestinal system. Side effects that occurred in patients in this study with a frequency of 1% or greater included nausea (18%), diarrhea/loose stools (14%), vomiting (7%), abdominal pain (7%), vaginitis (2%), dyspepsia (1%) and dizziness (1%). The majority of these complaints were mild in nature.

Pediatric Patients

Single- and Multiple-dose regimens: The types of side effects in pediatric patients were comparable to those seen in adults, with different incidence rates for the dosage regimens recommended in pediatric patients.

Acute Otitis Media: For the recommended total dosage regimen of 30 mg/kg, the most frequent side effects (≥ 1%) attributed to treatment were diarrhea, abdominal pain, vomiting, nausea and rash (see DOSAGE AND ADMINISTRATION and CLINICAL STUDIES, Pediatric Patients).

The incidence, based on dosing regimen, is described in the table below:

Dosage; Regimen | Diarrhea, % | Abdominal; Pain, % | Vomiting, % | Nausea, % | Rash, %
Dosage; Regimen | Diarrhea, % | Abdominal; Pain, % | Vomiting, % | Nausea, %
1 day | 4.3% | 1.4% | 4.9% | 1% | 1%
3 day | 2.6% | 1.7% | 2.3% | 0.4% | 0.6%
5 day | 1.8% | 1.2% | 1.1% | 0.5% | 0.4%

Community-Acquired Pneumonia: For the recommended dosage regimen of 10 mg/kg on Day 1 followed by 5 mg/kg on Days 2 to 5, the most frequent side effects attributed to treatment were diarrhea/loose stools, abdominal pain, vomiting, nausea and rash.

The incidence is described in the table below:

Dosage Regimen | Diarrhea/Loose stools, % | Abdominal Pain, % | Vomiting, % | Nausea, % | Rash, %
Dosage Regimen | Diarrhea/Loose stools, % | Abdominal Pain, % | Vomiting, % | Nausea, %
5 day | 5.8% | 1.9% | 1.9% | 1.9% | 1.6%

Pharyngitis/tonsillitis: For the recommended dosage regimen of 12 mg/kg on Days 1 to 5, the most frequent side effects attributed to treatment were diarrhea, vomiting, abdominal pain, nausea and headache.

The incidence is described in the table below:

Dosage Regimen | Diarrhea, % | AbdominalPain, % | Vomiting, % | Nausea, % | Rash, % | Headache, %
Dosage Regimen | Diarrhea, % | AbdominalPain, % | Vomiting, % | Nausea, % | Rash, %
5 day | 5.4% | 3.4% | 5.6% | 1.8% | 0.7% | 1.1%

With any of the treatment regimens, no other treatment-related side effects occurred in pediatric patients treated with azithromycin with a frequency greater than 1%. Side effects that occurred with a frequency of 1% or less included the following:

Cardiovascular: Chest pain.

Gastrointestinal: Dyspepsia, constipation, anorexia, enteritis, flatulence, gastritis, jaundice, loose stools and oral moniliasis.

Hematologic and Lymphatic: Anemia and leukopenia.

Nervous System: Headache (otitis media dosage), hyperkinesia, dizziness, agitation, nervousness and insomnia.

General: Fever, face edema, fatigue, fungal infection, malaise and pain.

Allergic: Rash and allergic reaction.

Respiratory: Cough increased, pharyngitis, pleural effusion and rhinitis.

Skin and Appendages: Eczema, fungal dermatitis, pruritus, sweating, urticaria and vesiculobullous rash.

Special Senses: Conjunctivitis.

Postmarketing Experience

Adverse events reported with azithromycin during the postmarketing period in adult and/or pediatric patients for which a causal relationship may not be established include:

Allergic: Arthralgia, edema, urticaria and angioedema.

Cardiovascular: Arrhythmias including ventricular tachycardia and hypotension. There have been rare reports of QT prolongation and torsade de pointes.

Gastrointestinal: Anorexia, constipation, dyspepsia, flatulence, vomiting/diarrhea rarely resulting in dehydration, pseudomembranous colitis, pancreatitis, oral candidiasis, pyloric stenosis, and rare reports of tongue discoloration.

General: Asthenia, paresthesia, fatigue, malaise and anaphylaxis (rarely fatal).

Genitourinary: Interstitial nephritis and acute renal failure and vaginitis.

Hematopoietic: Thrombocytopenia.

Liver/Biliary: Adverse reactions related to hepatic dysfunction have been reported in

postmarketing experience with azithromycin (see WARNINGS, Hepatotoxicity).

Nervous System: Convulsions, dizziness/vertigo, headache, somnolence, hyperactivity, nervousness, agitation and syncope.

Psychiatric: Aggressive reaction and anxiety.

Skin/Appendages: Pruritus, rarely serious skin reactions including erythema multiforme, Stevens-Johnson syndrome and toxic epidermal necrolysis.

Special Senses: Hearing disturbances including hearing loss, deafness and/or tinnitus and reports of taste/smell perversion and/or loss.

Laboratory Abnormalities

Adults

Clinically significant abnormalities (irrespective of drug relationship) occurring during the clinical trials were reported as follows: with an incidence of greater than 1%: decreased hemoglobin, hematocrit, lymphocytes, neutrophils and blood glucose; elevated serum creatine phosphokinase, potassium, ALT, GGT, AST, BUN, creatinine, blood glucose, platelet count, lymphocytes, neutrophils and eosinophils; with an incidence of less than 1%: leukopenia, neutropenia, decreased sodium, potassium, platelet count, elevated monocytes, basophils, bicarbonate, serum alkaline phosphatase, bilirubin, LDH and phosphate. The majority of subjects with elevated serum creatinine also had abnormal values at baseline.

When follow-up was provided, changes in laboratory tests appeared to be reversible.

In multiple-dose clinical trials involving more than 5000 patients, four patients discontinued therapy because of treatment-related liver enzyme abnormalities and one because of a renal function abnormality.

Pediatric Patients

One, Three and Five Day Regimens

Laboratory data collected from comparative clinical trials employing two 3 day regimens (30 mg/kg or 60 mg/kg in divided doses over 3 days), or two 5 day regimens (30 mg/kg or 60 mg/kg in divided doses over 5 days) were similar for regimens of azithromycin and all comparators combined, with most clinically significant laboratory abnormalities occurring at incidences of 1 to 5%. Laboratory data for patients receiving 30 mg/kg as a single dose were collected in one single center trial. In that trial, an absolute neutrophil count between 500 to 1500 cells/mm^3 was observed in 10/64 patients receiving 30 mg/kg as a single dose, 9/62 patients receiving 30 mg/kg given over 3 days, and 8/63 comparator patients. No patient had an absolute neutrophil count < 500 cells/mm^3 (see DOSAGE AND ADMINISTRATION).

In multiple-dose clinical trials involving approximately 4700 pediatric patients, no patients discontinued therapy because of treatment-related laboratory abnormalities.

DOSAGE AND ADMINISTRATION

See INDICATIONS AND USAGE and CLINICAL PHARMACOLOGY.

Adults

Infection [DUE TO THE INDICATED ORGANISMS (see INDICATIONS AND USAGE).] | Recommended Dose/Duration of Therapy
Community-acquired pneumonia (mild severity); Pharyngitis/tonsillitis (second line therapy); Skin/skin structure (uncomplicated) | 500 mg as a single dose on Day 1, followed; by 250 mg once daily on Days 2 through 5.
Acute bacterial exacerbations of chronic obstructive pulmonary disease (mild to moderate) | 500 mg QD x 3 days; OR; 500 mg as a single dose on Day 1, followed; by 250 mg once daily on Days 2 through 5.
Acute bacterial sinusitis | 500 mg QD x 3 days
Genital ulcer disease (chancroid) | One single 1 gram dose
Non-gonococcal urethritis and cervicitis | One single 1 gram dose
Gonococcal urethritis and cervicitis | One single 2 gram dose

Renal Insufficiency

No dosage adjustment is recommended for subjects with renal impairment (GFR ≤ 80 mL/min). The mean AUC0-120 was similar in subjects with GFR 10 to 80 mL/min compared to subjects with normal renal function, whereas it increased 35% in subjects with GFR < 10 mL/min compared to subjects with normal renal function. Caution should be exercised when azithromycin is administered to subjects with severe renal impairment (see CLINICAL PHARMACOLOGY, Special Populations, Renal Insufficiency).

Hepatic Insufficiency

The pharmacokinetics of azithromycin in subjects with hepatic impairment have not been established. No dose adjustment recommendations can be made in patients with impaired hepatic function (see CLINICALPHARMACOLOGY, Special Populations, Hepatic Insufficiency).

No dosage adjustment is recommended based on age or gender (see CLINICAL PHARMACOLOGY,Special Populations).

Pediatric Patients

Azithromycin for oral suspension can be taken with or without food.

Acute Otitis Media: The recommended dose of azithromycin for oral suspension for the treatment of pediatric patients with acute otitis media is 30 mg/kg given as a single dose or 10 mg/kg once daily for 3 days or 10 mg/kg as a single dose on the first day followed by 5 mg/kg/day on Days 2 through 5. (See chart below.)

Acute Bacterial Sinusitis: The recommended dose of azithromycin for oral suspension for the treatment of pediatric patients with acute bacterial sinusitis is 10 mg/kg once daily for 3 days. (See chart below.)

Community-Acquired Pneumonia: The recommended dose of azithromycin for oral suspension for the treatment of pediatric patients with community-acquired pneumonia is 10 mg/kg as a single dose on the first day followed by 5 mg/kg on Days 2 through 5. (See chart below.)

PEDIATRIC DOSAGE GUIDELINES FOR OTITIS MEDIA, ACUTE BACTERIAL SINUSITIS AND COMMUNITY-ACQUIRED PNEUMONIA (Age 6 months and above, see PRECAUTIONS, Pediatric Use.) Based on Body Weight
OTITIS MEDIA AND COMMUNITY-ACQUIRED PNEUMONIA: (5 Day Regimen) [Effectiveness of the 3 day or 1 day regimen in pediatric patients with community-acquired pneumonia has not been established.]
Dosing Calculated on 10 mg/kg/day Day 1 and 5 mg/kg/day Days 2 to 5.
Weight |  | 100 mg/5 mL |  | 200 mg/5 mL |  | Total mL per Treatment Course | Total mg per Treatment Course
Kg | Lbs. | Day 1 | Days 2 to 5 |  |  | Day 1 | Days 2 to 5
5 | 11 | 2.5 mL (½ tsp) | 1.25 mL (^1/4 tsp) |  |  | 7.5 mL | 150 mg
10 | 22 | 5 mL (1 tsp) | 2.5 mL (^1/2 tsp) |  |  | 15 mL | 300 mg
20 | 44 |  |  | 5 mL (1 tsp) | 2.5 mL (½ tsp) | 15 mL | 600 mg
30 | 66 |  |  | 7.5 mL (1½ tsp) | 3.75 mL (¾ tsp) | 22.5 mL | 900 mg
40 | 88 |  |  | 10 mL (2 tsp) | 5 mL (1 tsp) | 30 mL | 1200 mg
50 and above | 110 and above |  |  | 12.5 mL (2½ tsp) | 6.25 mL (1¼ tsp) | 37.5 mL | 1500 mg

OTITIS MEDIA AND ACUTE BACTERIAL SINUSITIS: (3 Day Regimen) [Effectiveness of the 5 day or 1 day regimen in pediatric patients with acute bacterial sinusitis has not been established.]
Dosing Calculated on 10 mg/kg/day.
Weight |  | 100 mg/5 mL | 200 mg/5 mL | Total mL per Treatment Course | Total mg per Treatment Course
Kg | Lbs. | Day 1 to 3 | Day 1 to 3 | Total mL per Treatment Course | Total mg per Treatment Course
5 | 11 | 2.5 mL; (½ tsp) |  | 7.5 mL | 150 mg
10 | 22 | 5 mL; (1 tsp) |  | 15 mL | 300 mg
20 | 44 |  | 5 mL; (1 tsp) | 15 mL | 600 mg
30 | 66 |  | 7.5 mL; (1½ tsp) | 22.5 mL | 900 mg
40 | 88 |  | 10 mL; (2 tsp) | 30 mL | 1200 mg
50 and above | 110 and above |  | 12.5 mL; (2½ tsp) | 37.5 mL | 1500 mg

OTITIS MEDIA: (1 Day Regimen)
Dosing Calculated on 30 mg/kg as a single dose.
Weight |  | 200 mg/5 mL | Total mL per Treatment Course | Total mg per Treatment Course
Kg | Lbs. | Day 1 | Total mL per Treatment Course | Total mg per Treatment Course
5 | 11 | 3.75 mL; (¾ tsp) | 3.75 mL | 150 mg
10 | 22 | 7.5 mL; (1½ tsp) | 7.5 mL | 300 mg
20 | 44 | 15 mL; (3 tsp) | 15 mL | 600 mg
30 | 66 | 22.5 mL; (4½ tsp) | 22.5 mL | 900 mg
40 | 88 | 30 mL; (6 tsp) | 30 mL | 1200 mg
50 and above | 110 and above | 37.5 mL; (7½ tsp) | 37.5 mL | 1500 mg

The safety of re-dosing azithromycin in pediatric patients who vomit after receiving 30 mg/kg as a single dose has not been established. In clinical studies involving 487 patients with acute otitis media given a single 30 mg/kg dose of azithromycin, eight patients who vomited within 30 minutes of dosing were re-dosed at the same total dose.

Pharyngitis/Tonsillitis: The recommended dose of azithromycin for oral suspension for children with pharyngitis/tonsillitis is 12 mg/kg once daily for 5 days. (See chart below.)

PEDIATRIC DOSAGE GUIDELINES FOR PHARYNGITIS/TONSILLITIS (Age 2 years and above, see PRECAUTIONS, Pediatric Use.) Based on Body Weight
PHARYNGITIS/TONSILLITIS: (5 Day Regimen)
Dosing Calculated on 12 mg/kg/day for 5 days.
Weight |  | 200 mg/5 mL | Total mL per Treatment Course | Total mg per; Treatment Course
Kg | Lbs. | Day 1 to 5 | Total mL per Treatment Course | Total mg per; Treatment Course
8 | 18 | 2.5 mL; (½ tsp) | 12.5 mL | 500 mg
17 | 37 | 5 mL; (1 tsp) | 25 mL | 1000 mg
25 | 55 | 7.5 mL; (1½ tsp) | 37.5 mL | 1500 mg
33 | 73 | 10 mL; (2 tsp) | 50 mL | 2000 mg
40 | 88 | 12.5 mL; (2½ tsp) | 62.5 mL | 2500 mg

Constituting instructions for azithromycin for oral suspension, 300, 600, 900, 1200 mg bottles. The table below indicates the volume of water to be used for constitution:

Amount of; water to be added | Total volume after constitution (azithromycin content) | Azithromycin concentration after constitution
9 mL (300 mg) | 15 mL (300 mg) | 100 mg/5 mL
9 mL (600 mg) | 15 mL (600 mg) | 200 mg/5 mL
12 mL (900 mg) | 22.5 mL (900 mg) | 200 mg/5 mL
15 mL (1200 mg) | 30 mL (1200 mg) | 200 mg/5 mL

Shake well before each use. Oversized bottle provides shake space. Keep tightly closed.

After mixing, store suspension at 5° to 25°C (41° to 77°F) and use within 10 days. Discard after full dosing is completed.

HOW SUPPLIED

Azithromycin for oral suspension USP after constitution contains a flavored pink suspension. Azithromycin for oral suspension USP is supplied to provide 200 mg/5 mL suspension in bottles as follows:

200mg/5ml Suspension 15ml NDC (63187-093-15)

200mg/5ml Suspension 22.5ml NDC (63187-093-22)

200mg/5ml Suspension 30ml NDC (63187-093-30)

BOXED WARNING

Azithromycin contents per bottle

600 mg

See DOSAGE AND ADMINISTRATIONfor constitution instructions with each bottle type.

Storage: Store dry powder at 20° to 25°C (68° to 77°F)[See USP Controlled Room Temperature]. Store constituted suspension between 5° to 25°C (41° to 77°F) and discard when full dosing is completed.

KEEP THIS AND ALL MEDICATIONS OUT OF THE REACH OF CHILDREN.

CLINICAL STUDIES

See INDICATIONS AND USAGEand Pediatric Use.

Pediatric Patients

From the perspective of evaluating pediatric clinical trials, Days 11 to 14 were considered on-therapy evaluations because of the extended half-life of azithromycin. Day 11 to 14 data are provided for clinical guidance. Day 24 to 32 evaluations were considered the primary test of cure endpoint.

Acute Otitis Media

Safety and efficacy using azithromycin 30 mg/kg given over 5 days

Protocol 1

In a double-blind, controlled clinical study of acute otitis media performed in the United States, azithromycin (10 mg/kg on Day 1 followed by 5 mg/kg on Days 2 to 5) was compared to amoxicillin/clavulanate potassium (4:1). For the 553 patients who were evaluated for clinical efficacy, the clinical success rate (i.e., cure plus improvement) at the Day 11 visit was 88% for azithromycin and 88% for the control agent. For the 521 patients who were evaluated at the Day 30 visit, the clinical success rate was 73% for azithromycin and 71% for the control agent.

In the safety analysis of the above study, the incidence of treatment-related adverse events, primarily gastrointestinal, in all patients treated was 9% with azithromycin and 31% with the control agent. The most common side effects were diarrhea/loose stools (4% azithromycin vs. 20% control), vomiting (2% azithromycin vs. 7% control), and abdominal pain (2% azithromycin vs. 5% control).

Protocol 2

In a non-comparative clinical and microbiologic trial performed in the United States, where significant rates of beta-lactamase producing organisms (35%) were found, 131 patients were evaluable for clinical efficacy. The combined clinical success rate (i.e., cure and improvement) at the Day 11 visit was 84% for azithromycin. For the 122 patients who were evaluated at the Day 30 visit, the clinical success rate was 70% for azithromycin.

Microbiologic determinations were made at the pre-treatment visit. Microbiology was not reassessed at later visits. The following presumptive bacterial/clinical cure outcomes (i.e., clinical success) were obtained from the evaluable group:

Presumed Bacteriologic Eradication

 | Day 11; Azithromycin | Day 30; Azithromycin
S. pneumoniae | 61/74 (82%) | 40/56 (71%)
H. influenzae | 43/54 (80%) | 30/47 (64%)
M. catarrhalis | 28/35 (80%) | 19/26 (73%)
S. pyogenes | 11/11 (100%) | 7/7
Overall | 177/217 (82%) | 97/137 (73%)

In the safety analysis of this study, the incidence of treatment-related adverse events, primarily gastrointestinal, in all patients treated was 9%. The most common side effect was diarrhea (4%).

Protocol 3

In another controlled comparative clinical and microbiologic study of otitis media performed in the United States, azithromycin was compared to amoxicillin/clavulanate potassium (4:1). This study utilized two of the same investigators as Protocol 2 (above), and these two investigators enrolled 90% of the patients in Protocol 3. For this reason, Protocol 3 was not considered to be an independent study. Significant rates of beta-lactamase producing organisms (20%) were found. Ninety-two (92) patients were evaluable for clinical and microbiologic efficacy. The combined clinical success rate (i.e., cure and improvement) of those patients with a baseline pathogen at the Day 11 visit was 88% for azithromycin vs. 100% for control; at the Day 30 visit, the clinical success rate was 82% for azithromycin vs. 80% for control.

Microbiologic determinations were made at the pre-treatment visit. Microbiology was not reassessed at later visits. At the Day 11 and Day 30 visits, the following presumptive bacterial/clinical cure outcomes (i.e., clinical success) were obtained from the evaluable group:

Presumed Bacteriologic Eradication

 | Day 11 |  | Day 30
 | Azithromycin | Control | Azithromycin | Control
S. pneumoniae | 25/29 (86%) | 26/26 (100%) | 22/28 (79%) | 18/22 (82%)
H. influenzae | 9/11 (82%) | 9/9 | 8/10 (80%) | 6/8
M. catarrhalis | 7/7 | 5/5 | 5/5 | 2/3
S. pyogenes | 2/2 | 5/5 | 2/2 | 4/4
Overall | 43/49 (88%) | 45/45 (100%) | 37/45 (82%) | 30/37 (81%)

In the safety analysis of the above study, the incidence of treatment-related adverse events, primarily gastrointestinal, in all patients treated was 4% with azithromycin and 31% with the control agent. The most common side effect was diarrhea/loose stools (2% azithromycin vs. 29% control).

Safety and efficacy using azithromycin 30 mg/kg given over 3 days

Protocol 4

In a double-blind, controlled, randomized clinical study of acute otitis media in pediatric patients from 6 months to 12 years of age, azithromycin (10 mg/kg per day for 3 days) was compared to amoxicillin/clavulanate potassium (7:1) in divided doses q12h for 10 days. Each patient received active drug and placebo matched for the comparator.

For the 366 patients who were evaluated for clinical efficacy at the Day 12 visit, the clinical success rate (i.e., cure plus improvement) was 83% for azithromycin and 88% for the control agent. For the 362 patients who were evaluated at the Day 24 to 28 visit, the clinical success rate was 74% for azithromycin and 69% for the control agent.

In the safety analysis of the above study, the incidence of treatment-related adverse events, primarily gastrointestinal, in all patients treated was 10.6% with azithromycin and 20% with the control agent. The most common side effects were diarrhea/loose stools (5.9% azithromycin vs. 14.6% control), vomiting (2.1% azithromycin vs. 1.1% control), and rash (0% azithromycin vs. 4.3% control).

Safety and efficacy using azithromycin 30 mg/kg given as a single dose

Protocol 5

A double-blind, controlled, randomized trial was performed at nine clinical centers. Pediatric patients from 6 months to 12 years of age were randomized 1:1 to treatment with either azithromycin (given at 30 mg/kg as a single dose on Day 1) or amoxicillin/clavulanate potassium (7:1), divided q12h for 10 days. Each child received active drug, and placebo matched for the comparator.

Clinical response (Cure, Improvement, Failure) was evaluated at End of Therapy (Day 12 to 16) and Test of Cure (Day 28 to 32). Safety was evaluated throughout the trial for all treated subjects. For the 321 subjects who were evaluated at End of Treatment, the clinical success rate (cure plus improvement) was 87% for azithromycin, and 88% for the comparator. For the 305 subjects who were evaluated at Test of Cure, the clinical success rate was 75% for both azithromycin and the comparator.

In the safety analysis, the incidence of treatment-related adverse events, primarily gastrointestinal, was 16.8% with azithromycin, and 22.5% with the comparator. The most common side effects were diarrhea (6.4% with azithromycin vs. 12.7% with the comparator), vomiting (4% with each agent), rash (1.7% with azithromycin vs. 5.2% with the comparator) and nausea (1.7% with azithromycin vs. 1.2% with the comparator).

Protocol 6

In a non-comparative clinical and microbiological trial, 248 patients from 6 months to 12 years of age with documented acute otitis media were dosed with a single oral dose of azithromycin (30 mg/kg on Day 1).

For the 240 patients who were evaluable for clinical modified Intent-to-Treat (MITT) analysis, the clinical success rate (i.e., cure plus improvement) at Day 10 was 89% and for the 242 patients evaluable at Day 24 to 28, the clinical success rate (cure) was 85%.

Presumed Bacteriologic Eradication

 | Day 10 | Day 24 to 28
S. pneumoniae | 70/76 (92%) | 67/76 (88%)
H. influenzae | 30/42 (71%) | 28/44 (64%)
M. catarrhalis | 10/10 (100%) | 10/10 (100%)
Overall | 110/128 (86%) | 105/130 (81%)

In the safety analysis of this study, the incidence of treatment-related adverse events, primarily gastrointestinal, in all the subjects treated was 12.1%. The most common side effects were vomiting (5.6%), diarrhea (3.2%), and abdominal pain (1.6%).

Pharyngitis/Tonsillitis

In three double-blind controlled studies, conducted in the United States, azithromycin (12 mg/kg once a day for 5 days) was compared to penicillin V (250 mg three times a day for 10 days) in the treatment of pharyngitis due to documented Group A β-hemolytic streptococci (GABHS or S. pyogenes). Azithromycin was clinically and microbiologically statistically superior to penicillin at Day 14 and Day 30 with the following clinical success (i.e., cure and improvement) and bacteriologic efficacy rates (for the combined evaluable patient with documented GABHS):

Three U.S. Streptococcal Pharyngitis Studies

Azithromycin vs. Penicillin V

EFFICACY RESULTS

 | Day 14 | Day 30
Bacteriologic Eradication:
Azithromycin | 323/340 (95%) | 255/330 (77%)
Penicillin V | 242/332 (73%) | 206/325 (63%)
Clinical Success (Cure plus improvement):
Azithromycin | 336/343 (98%) | 310/330 (94%)
Penicillin V | 284/338 (84%) | 241/325 (74%)

Approximately 1% of azithromycin-susceptible S. pyogenes isolates were resistant to azithromycin following therapy.

The incidence of treatment-related adverse events, primarily gastrointestinal, in all patients treated was 18% on azithromycin and 13% on penicillin. The most common side effects were diarrhea/loose stools (6% azithromycin vs. 2% penicillin), vomiting (6% azithromycin vs. 4% penicillin), and abdominal pain (3% azithromycin vs. 1% penicillin).

Adult Patients

Acute Bacterial Exacerbations of Chronic Obstructive Pulmonary Disease

In a randomized, double-blind controlled clinical trial of acute exacerbation of chronic bronchitis (AECB), azithromycin (500 mg once daily for 3 days) was compared with clarithromycin (500 mg twice daily for 10 days). The primary endpoint of this trial was the clinical cure rate at Day 21 to 24. For the 304 patients analyzed in the modified intent to treat analysis at the Day 21 to 24 visit, the clinical cure rate for 3 days of azithromycin was 85% (125/147) compared to 82% (129/157) for 10 days of clarithromycin.

The following outcomes were the clinical cure rates at the Day 21 to 24 visit for the bacteriologically evaluable patients by pathogen:

Pathogen | Azithromycin | Clarithromycin
 | (3 Days) | (10 Days)
S. pneumoniae | 29/32 (91%) | 21/27 (78%)
H. influenzae | 12/14 (86%) | 14/16 (88%)
M. catarrhalis | 11/12 (92%) | 12/15 (80%)

In the safety analysis of this study, the incidence of treatment-related adverse events, primarily gastrointestinal, were comparable between treatment arms (25% with azithromycin and 29% with clarithromycin). The most common side effects were diarrhea, nausea and abdominal pain with comparable incidence rates for each symptom of 5 to 9% between the two treatment arms (see ADVERSE REACTIONS).

Acute Bacterial Sinusitis

In a randomized, double-blind, double-dummy controlled clinical trial of acute bacterial sinusitis, azithromycin (500 mg once daily for 3 days) was compared with amoxicillin/clavulanate (500/125 mg tid for 10 days). Clinical response assessments were made at Day 10 and Day 28. The primary endpoint of this trial was prospectively defined as the clinical cure rate at Day 28. For the 594 patients analyzed in the modified intent to treat analysis at the Day 10 visit, the clinical cure rate for 3 days of azithromycin was 88% (268/303) compared to 85% (248/291) for 10 days of amoxicillin/clavulanate. For the 586 patients analyzed in the modified intent to treat analysis at the Day 28 visit, the clinical cure rate for 3 days of azithromycin was 71.5% (213/298) compared to 71.5% (206/288), with a 97.5% confidence interval of -8.4 to 8.3, for 10 days of amoxicillin/clavulanate.

In the safety analysis of this study, the overall incidence of treatment-related adverse events, primarily gastrointestinal, was lower in the azithromycin treatment arm (31%) than in the amoxicillin/clavulanate arm (51%). The most common side effects were diarrhea (17% in the azithromycin arm vs. 32% in the amoxicillin/clavulanate arm), and nausea (7% in the azithromycin arm vs. 12% in the amoxicillin/clavulanate arm) (see ADVERSE REACTIONS).

In an open label, noncomparative study requiring baseline transantral sinus punctures the following outcomes were the clinical success rates at the Day 7 and Day 28 visits for the modified intent to treat patients administered 500 mg of azithromycin once daily for 3 days with the following pathogens:

Pathogen | Azithromycin (500 mg per day for 3 Days)
 | Day 7 | Day 28
S. pneumoniae | 23/26 (88%) | 21/25 (84%)
H. influenzae | 28/32 (87%) | 24/32 (75%)
M. catarrhalis | 14/15 (93%) | 13/15 (87%)

The overall incidence of treatment-related adverse events in the noncomparative study was 21% in modified intent to treat patients treated with azithromycin at 500 mg once daily for 3 days with the most common side effects being diarrhea (9%), abdominal pain (4%) and nausea (3%) (see ADVERSE REACTIONS).

ANIMAL TOXICOLOGY

Phospholipidosis (intracellular phospholipid accumulation) has been observed in some tissues of mice, rats, and dogs given multiple doses of azithromycin. It has been demonstrated in numerous organ systems (e.g., eye, dorsal root ganglia, liver, gallbladder, kidney, spleen, and pancreas) in dogs treated with azithromycin at doses which, expressed on the basis of mg/ m^2, are approximately equal to the recommended adult human dose, and in rats treated at doses approximately one-sixth of the recommended adult human dose. This effect has been shown to be reversible after cessation of azithromycin treatment. Phospholipidosis has been observed to a similar extent in the tissues of neonatal rats and dogs given daily doses of azithromycin ranging from 10 days to 30 days. Based on the pharmacokinetic data, phospholipidosis has been seen in the rat (30 mg/kg dose) at observed Cmax value of 1.3 mcg/mL (six times greater than the observed Cmax of 0.216 mcg/mL at the pediatric dose of 10 mg/kg). Similarly, it has been shown in the dog (10 mg/kg dose) at observed Cmax value of 1.5 mcg/mL (seven times greater than the observed same Cmax and drug dose in the studied pediatric population). On a mg/m^2 basis, 30 mg/kg dose in the neonatal rat (135 mg/m^2) and 10 mg/kg dose in the neonatal dog (79 mg/m^2) are approximately 0.5 and 0.3 times, respectively, the recommended dose in the pediatric patients with an average body weight of 25 kg. Phospholipidosis, similar to that seen in the adult animals, is reversible after cessation of azithromycin treatment. The significance of these findings for animals and for humans is unknown.

REFERENCES

- Clinical and Laboratory Standards Institute (CLSI). Methods for Dilution Antimicrobial Susceptibility Tests for Bacteria that Grow Aerobically; Approved Standard - Ninth Edition. CLSI document M07-A9. CLSI 950 West Valley Rd, Suite 250, Wayne, PA 19087, 2012.
- CLSI, Performance Standards for Antimicrobial Susceptibility Testing; Twenty-Second Informational Supplement. CLSI document M100-S22. CLSI, Wayne, PA 19087, 2012.
- CLSI. Performance Standards for Antimicrobial Disk Susceptibility Tests; Approved Standard - Eleventh Edition. CLSI document M02-A11. CLSI, Wayne, PA 19087, 2012.

Manufactured In Croatia By:

PLIVA HRVATSKA d.o.o.
Zagreb, Croatia

Manufactured For:

TEVA PHARMACEUTICALS USA
Sellersville, PA 18960

Rev. E 2/2013

Relabeled by:

PROFICIENT RX LP
Thousand Oaks, CA 91320

PATIENT SUMMARY OF INFORMATION ABOUT

Azithromycin For Oral Suspension USP

Cherry-flavored suspension

Rx Only

This summary contains important information about azithromycin. It is not meant to take the place of your child’s doctor’s instructions. Read this information carefully before you give azithromycin to your child. Ask your child’s doctor, nurse or pharmacist if you do not understand any of this information or if you want to know more about azithromycin.

• What Is Azithromycin?

Azithromycin is an antibiotic medicine that is taken only once a day to treat the following types of infections in children: ear infections, pneumonia, and throat infections.

• Can Antibiotics Cure A Cold Or Flu?

No. Antibiotics work only on infections caused by bacteria. They do not kill viruses. No antibiotic, including azithromycin, can treat viral infections such as the common cold and the flu.

• What To Tell Your Child’s Doctor Before You Start Azithromycin

Only your child’s doctor can decide if azithromycin is right for your child. Before you start azithromycin, be sure to tell the doctor if your child:

- is being given any prescription medicines, including those for asthma
- is being given any over-the-counter medicines you can buy without a prescription, including natural/herbal remedies
- has ever had any liver or kidney problems
- has any other medical problems
- is allergic to any medicines
- is allergic to certain antibiotics such as erythromycin
- is allergic to azithromycin or any of the ingredients of azithromycin suspension. Your doctor or pharmacist can give you a list of these ingredients.

• Azithromycin And Other Medicines

Some medicines can affect how well azithromycin works. Check with your child’s doctor before giving your child any new medicines.

• What Is The Right Amount Of Azithromycin To Give To My Child?

Azithromycin gets deep into infected tissue where it is released slowly over time so the medicine keeps fighting bacteria for many days after the last dose is taken. This is why azithromycin may be taken for as short a time as one day. Your child’s doctor will decide the total amount of azithromycin to give to your child, depending on your child’s weight and on the specific infection your child has. In addition to deciding the total amount of azithromycin to give to your child, the doctor will tell you to give all the medicine to your child in 1 day or to divide it over 3 days or over 5 days.

For Ear lnfections

For ear infections, your child’s doctor will tell you to give azithromycin to your child in one of the following ways: the total amount as 1 dose on 1 day, or the total amount divided into 1 dose per-day for 3 days or the total amount divided into 1 dose-per-day for 5 days, with a double dose on the first day. Whether given all on 1 day, or divided over 3 days or over 5 days, the total amount of azithromycin you give to your child should be the same.

For Pneumonia

For pneumonia, your child’s doctor will tell you to give azithromycin to your child by dividing the total amount into 1 dose-per-day for 5 days, with a double dose on the first day.

For Throat lnfections (“strep throat”)

For throat infections, your child’s doctor will tell you to give azithromycin to your child by dividing the total amount into 1 dose-per-day for 5 days. When you give azithromycin for 5 days for throat infections, you do not need to give a double dose on the first day (as you would with ear infections).
If you have questions about how to give azithromycin to your child, please ask your child’s doctor, nurse or pharmacist.

• How And When To Give Azithromycin

Azithromycin may be taken with or without food and may be taken at any time of day.
Shake the bottle well just before you give a dose.
Give azithromycin for the full number of days prescribed by the doctor, even if your child feels better before finishing all the medicine as prescribed.
If you forget to give your child a dose, call the doctor.

• When Can I Expect My Child To Begin Feeling Better?

Although azithromycin’s dosing is short and you may be able to give all the medicine to your child more easily, you should not expect azithromycin to work faster than other antibiotics which are dosed for up to 10 days.
Your child’s doctor or nurse can advise you when your child should begin feeling better.

• Possible Side Effects

Like all medicines, azithromycin may cause side effects in some children that are usually mild to moderate and go away after the medicine is stopped. The most common ones are diarrhea, abdominal (“tummy”) pain, vomiting and nausea.

As with other antibiotics, if your child develops diarrhea that becomes severe and watery or does not go away, stop taking the medicine and call the doctor or nurse. This could be a sign of a serious medical problem.
Allergic reactions to azithromycin are rare, but these can be very serious if not treated right away by a doctor. If you think your child might be having an allergic reaction to azithromycin, stop the medicine and call the doctor right away. If you cannot reach the doctor, go to the nearest hospital emergency room. Symptoms of a severe allergic reaction may include trouble breathing; swelling of the face, mouth and neck; or severe skin rash or blisters.
Azithromycin may cause other less common side effects besides those listed here. For a list of all the side effects that have been reported, ask the doctor, nurse or pharmacist for the Azithromycin Professional Package Insert.

• What Should I Do If My Child Vomits (Spits Up) The 1 Day Treatment of Azithromycin?

If your child vomits within 30 minutes after the 1 day treatment for an ear infection, please call your child’s doctor.

• What To Do For An Overdose

In case of accidental overdose, call your child’s doctor right away or go to the nearest emergency room.

• How To Store Azithromycin

Keep azithromycin out of the reach of children. Azithromycin can be stored at room temperature. You do not have to keep it in the refrigerator. Throw away any medicine that is left over after treatment.

Manufactured in Croatia By:

PLIVA HRVATSKA d.o.o.
Zagreb, Croatia

Manufactured For:

TEVA PHARMACEUTICALS USA
Sellersville, PA 18960

Rev. A 6/2012

Relabeled by:

PROFICIENT RX LP
Thousand Oaks, CA 91320